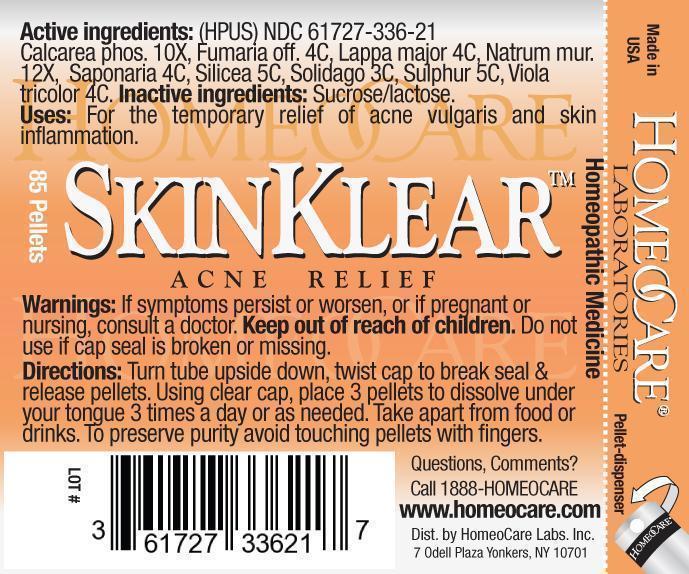 DRUG LABEL: Skin Klear Acne Relief
NDC: 61727-336 | Form: PELLET
Manufacturer: Homeocare Laboratories
Category: homeopathic | Type: HUMAN OTC DRUG LABEL
Date: 20181231

ACTIVE INGREDIENTS: TRIBASIC CALCIUM PHOSPHATE 10 [hp_X]/4 g; FUMARIA OFFICINALIS FLOWERING TOP 4 [hp_C]/4 g; ARCTIUM LAPPA ROOT 4 [hp_C]/4 g; SODIUM CHLORIDE 12 [hp_X]/4 g; SAPONARIA OFFICINALIS ROOT 4 [hp_C]/4 g; SILICON DIOXIDE 5 [hp_C]/4 g; SOLIDAGO VIRGAUREA FLOWERING TOP 3 [hp_C]/4 g; SULFUR 5 [hp_C]/4 g; VIOLA TRICOLOR 4 [hp_C]/4 g
INACTIVE INGREDIENTS: SUCROSE; LACTOSE

Skin Klear Acne Relief

Active ingredients:

Calcarea phos. 10X, Fumaria off. 4C, Lappa major 4C, Natrum mur. 12X, Saponaria 4C, Silicea 5C, Solidago 3C, Sulphur 5C, Viola tricolor 4C.

Inactive ingredients:

Sucrose/lactose.

Purpose:

For the temporary relief of acne vulgaris and skin inflammation.

Keep out of reach of children.

Indications & Usage:

Turn tube upside down, twist cap to break seal & release pellets. Using clear cap, place 3 pellets to dissolve under your tongue 3 times a day or as needed. Take apart from food or drinks. To preserve purity avoid touching pellets with fingers.

Warnings:

If symptoms persist or worsen, or if pregnant or nursing, consult a doctor. Keep out of reach of children. Do not use if cap seal is broken or missing.

Dosage & Administration:

Turn tube upside down, twist cap to break seal & release pellets. Using clear cap, place 3 pellets to dissolve under your tongue 3 times a day or as needed. Take apart from food or drinks. To preserve purity avoid touching pellets with fingers.

Skin Klear Acne Relief

Homeopathic Medicine

85 Pellets

hcl_label_SkinKlear-2012.jpg